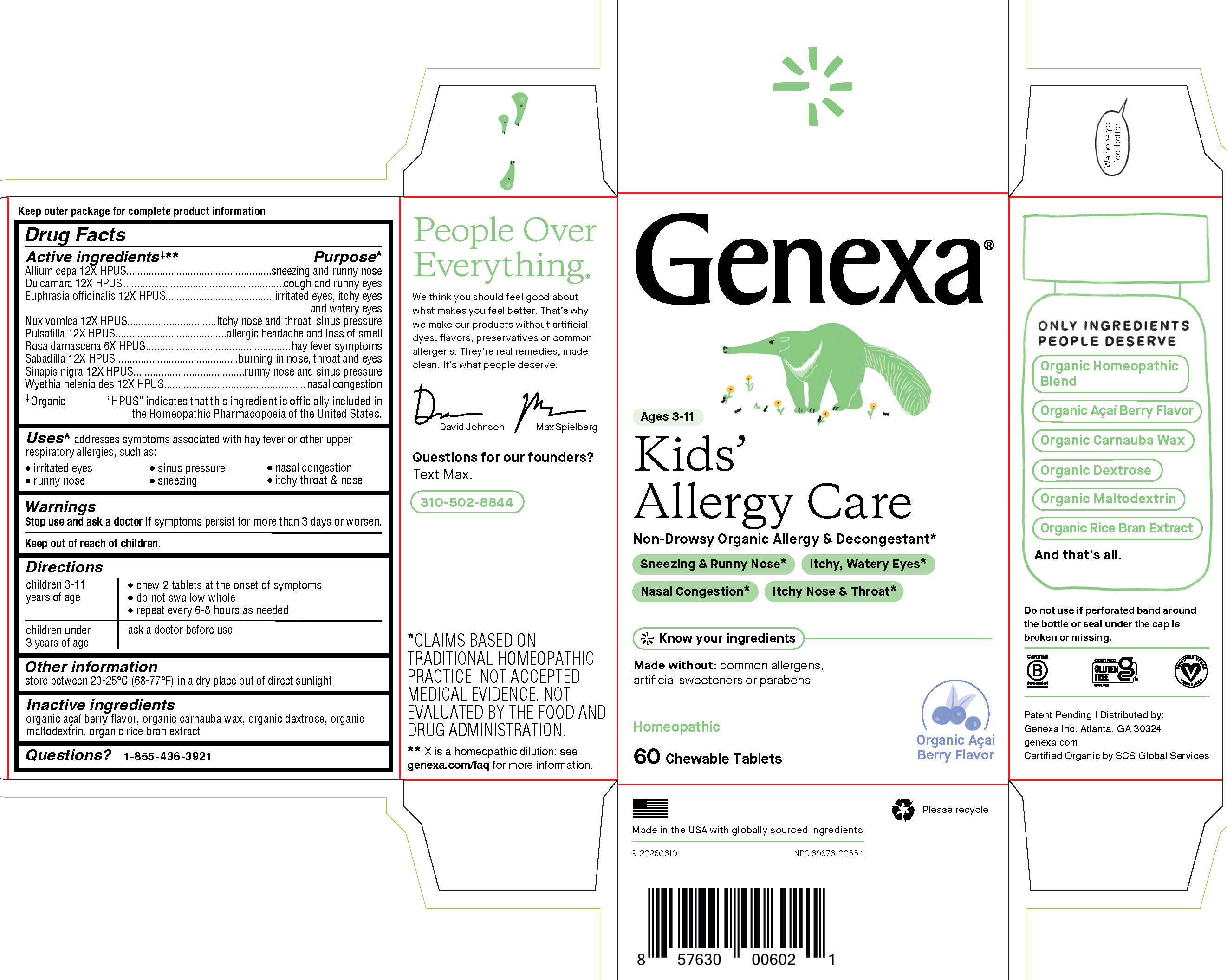 DRUG LABEL: Genexa Kids Allergy Care
NDC: 69676-0055 | Form: TABLET, CHEWABLE
Manufacturer: Genexa Inc.
Category: homeopathic | Type: HUMAN OTC DRUG LABEL
Date: 20251215

ACTIVE INGREDIENTS: EUPHRASIA STRICTA 12 [hp_X]/1 1; PULSATILLA PRATENSIS 12 [hp_X]/1 1; SCHOENOCAULON OFFICINALE SEED 12 [hp_X]/1 1; SOLANUM DULCAMARA STEM 12 [hp_X]/1 1; ONION 12 [hp_X]/1 1; STRYCHNOS NUX-VOMICA SEED 12 [hp_X]/1 1; ROSA DAMASCENA FLOWERING TOP 6 [hp_X]/1 1; BLACK MUSTARD SEED 12 [hp_X]/1 1; WYETHIA HELENIOIDES ROOT 12 [hp_X]/1 1
INACTIVE INGREDIENTS: ACAI; CARNAUBA WAX; MALTODEXTRIN; RICE BRAN; DEXTROSE

KIDS' ALLERGY CARE

Drug Facts

Active ingredients‡**

Allium cepa 12X HPUS

Dulcamara 12X HPUS

Euphrasia officinalis 12X HPUS

Nux vomica 12X HPUS

Pulsatilla 12X HPUS

Rosa damascena 6X HPUS

Sabadilla 12X HPUS

Sinapis nigra 12X HPUS

Wyethia helenioides 12X HPUS

‡ Organic

"HPUS" indicates that this ingredient is officially included in the Homeopathic Pharmacopoeia of the United States.

Purpose*

sneezing and runny nose

cough and runny eyes

irritated eyes, itchy eyes and watery eyes

itchy nose and throat, sinus pressure

allergic headache and loss of smell

hay fever symptoms

burning in nose, throat and eyes

runny nose and sinus pressure

nasal congestion

Uses*

addresses symptoms associated with hay fever or other upper respiratory allergies, such as:

- irritated eyes
- sinus pressure
- nasal congestion
- runny nose
- sneezing
- itchy throat & nose

Warnings

Stop use and ask a doctor if symptoms persist for more than 3 days or worsen.

Keep out of reach of children.

Directions

children 3-11 years of age | - chew 2 tablets at the onset of symptoms - do not swallow whole - repeat every 6-8 hours as needed
children under 3 years of age | ask a doctor before use

Other information

store between 20-25° C (68-77° F) in a dry place out of direct sunlight

Inactive ingredients

organic açaÍ berry flavor, organic carnauba wax, organic dextrose, organic maltodextrin, organic rice bran extract

Questions?

1-855-436-3921

* CLAIMS BASED ON TRADITIONAL HOMEOPATHIC PRACTICE, NOT ACCEPTED MEDICAL EVIDENCE. NOT EVALUATED BY THE FOOD AND DRUG ADMINISTRATION.

** X is a homeopathic dilution; see genexa.com/faq for more information.

Do not use if perforated band around the bottle or seal under the cap is broken or missing.

Patent Pending | Distributed by:

Genexa Inc. Atlanta, GA 30324

genexa.com

Certified Organic by SCS Global Services

Made in the USA with globally sourced ingredients.

NDC 69676-0055-1

PACKAGE LABEL

Genexa®

Ages 3-11

Kids' Allergy Care

Non-Drowsy Organic Allergy & Decongestant*

Sneezing & Runny Nose*

Itchy, Watery Eyes*

Nasal Congestion*

Itchy Nose & Throat*

Know your ingredients

Made without: common allergens, artificial sweeteners or parabens

Homeopathic

60 Chewable Tablets

Organic AçaÍ Berry Flavor